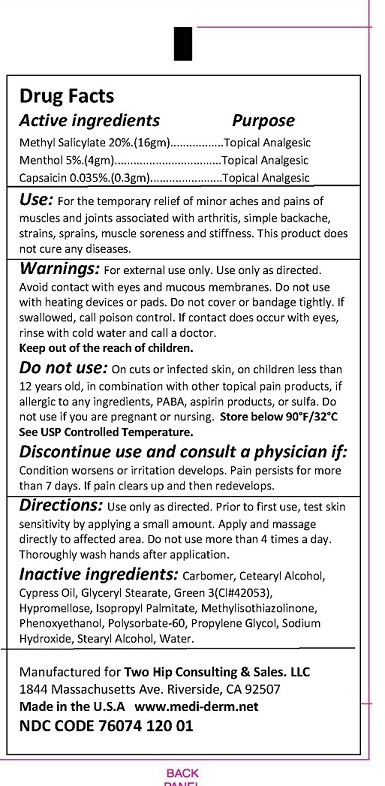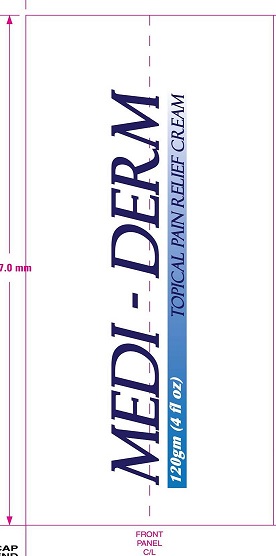 DRUG LABEL: Topical
NDC: 76074-120 | Form: CREAM
Manufacturer: Two Hip Consulting, LLC
Category: otc | Type: HUMAN OTC DRUG LABEL
Date: 20190208

ACTIVE INGREDIENTS: METHYL SALICYLATE 20 g/100 g; MENTHOL 5 g/100 g; CAPSAICIN .0355 g/100 g
INACTIVE INGREDIENTS: CARBOMER HOMOPOLYMER TYPE B (ALLYL SUCROSE CROSSLINKED); CETOSTEARYL ALCOHOL; GLYCERYL MONOSTEARATE; FD&C GREEN NO. 3; HYPROMELLOSE 2208 (100000 MPA.S); ISOPROPYL PALMITATE; METHYLISOTHIAZOLINONE; PHENOXYETHANOL; POLYSORBATE 60; PROPYLENE GLYCOL; SODIUM HYDROXIDE; STEARYL ALCOHOL; WATER

ACTIVE INGREDIENTS

Methyl salicylate 20% (16gm)

Menthol 5% (4 gm)

Capsaicin 0.035% (0.3gm)

PURPOSE

TOPICAL ANALGESIC

USES

For the temporary relief of minor aches and pains of muscles and joints associated with arthritis, simple backache, strains, sprains, muscle soreness and stiffness. This product does not cure any diseases.

WARNINGS

Warnings: For external use only. Use only as directed. Avoid contact with eyes and mucous membranes. Do not use with heating devices or pads. Do not cover or bandage tightly. If swallowed, call poison control. If contact does occur with eyes rinse with cold water and call a doctor.

Discontinue use and consult a physician if condition worsens or irritation develops. Pain persists for more than 7 days. If pain clears up and then redevelops.

Do not use: on cuts or infected skin, on children less than 12 years old, in combination with other topical pain products, if allergic to any ingredients, PABA, aspirin products, or sulfa. Do not use if you are pregnant or nursing. Store below 90 degrees F/32 degrees C. See USP Controlled Temperature.

KEEP OUT OF REACH OF CHILDREN.

DIRECTIONS

Use only as directed. Prior to first use, test skin sensitivity by applying a small amount. Apply and massage directly to affected area. Do not use more than 4 times a day. Thoroughly wash hands after application.

Inactive Ingredients

Carbomer, Cetearyl Alcohol, Cypress Oil, Glyceryl Stearate, Green 3 (CI# 42053), Hypromellose, Isopropyl Palmitate, Methylisothiazolinone, Phenoxyethanol, Polysorbate-60, Propylene Glycol, sodium Hydroxide, Stearyl Alcohol, Water.